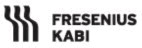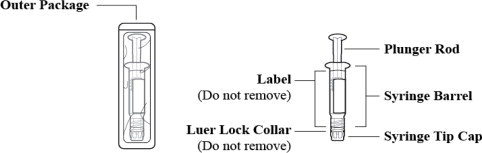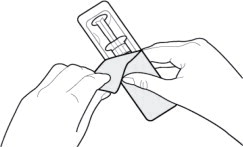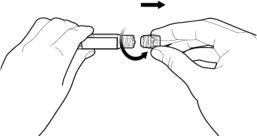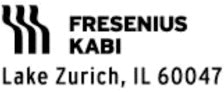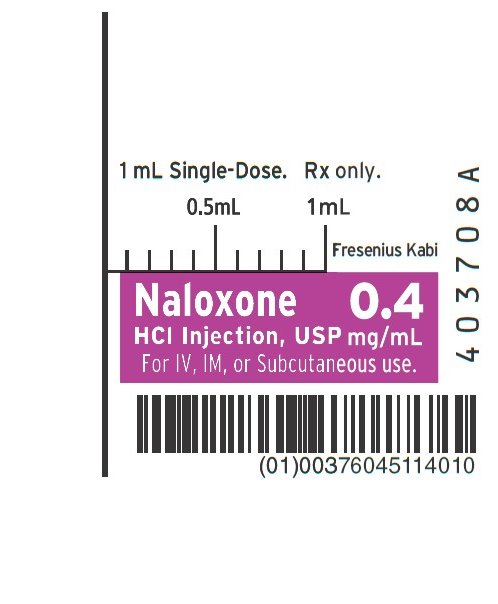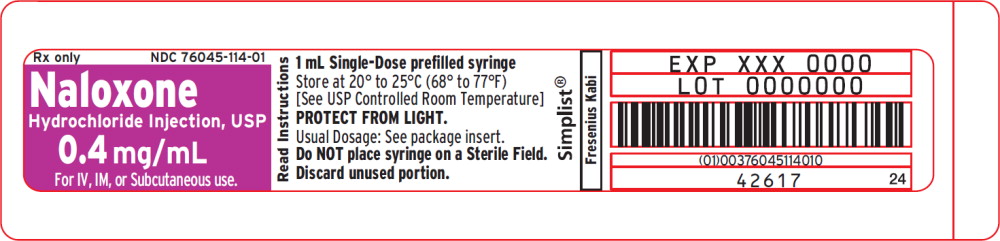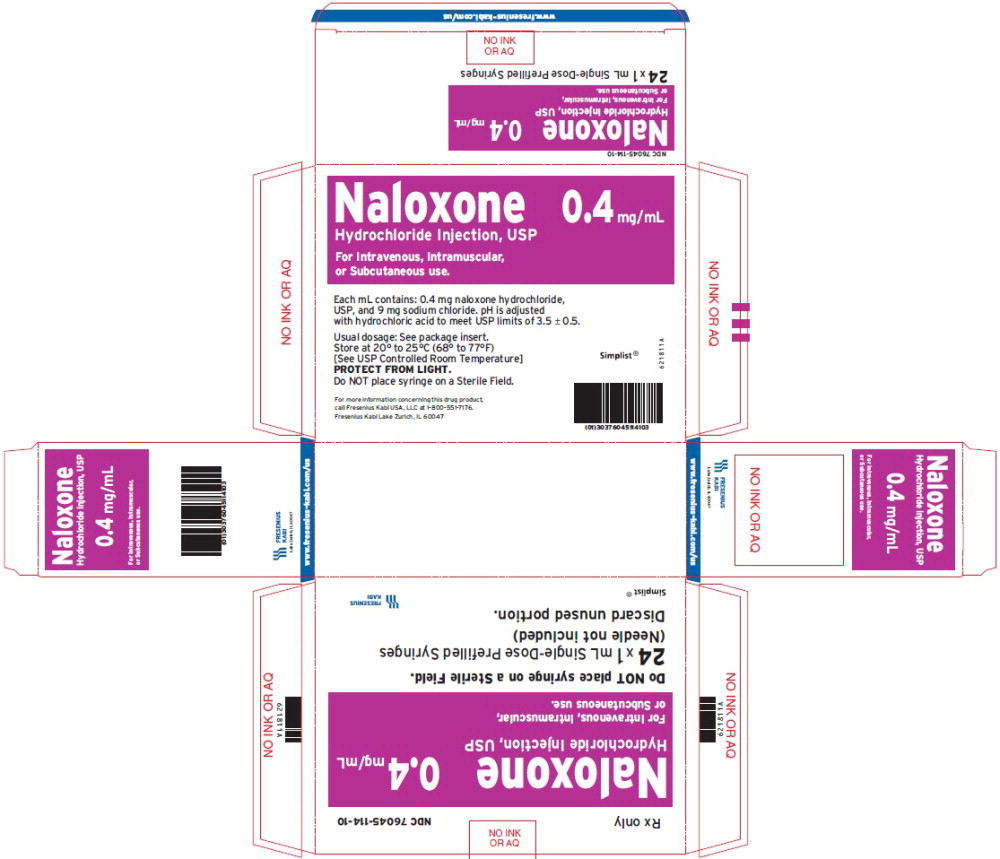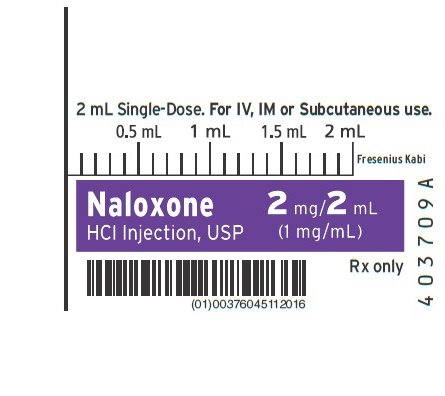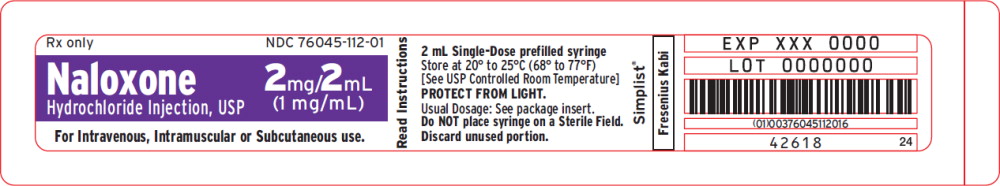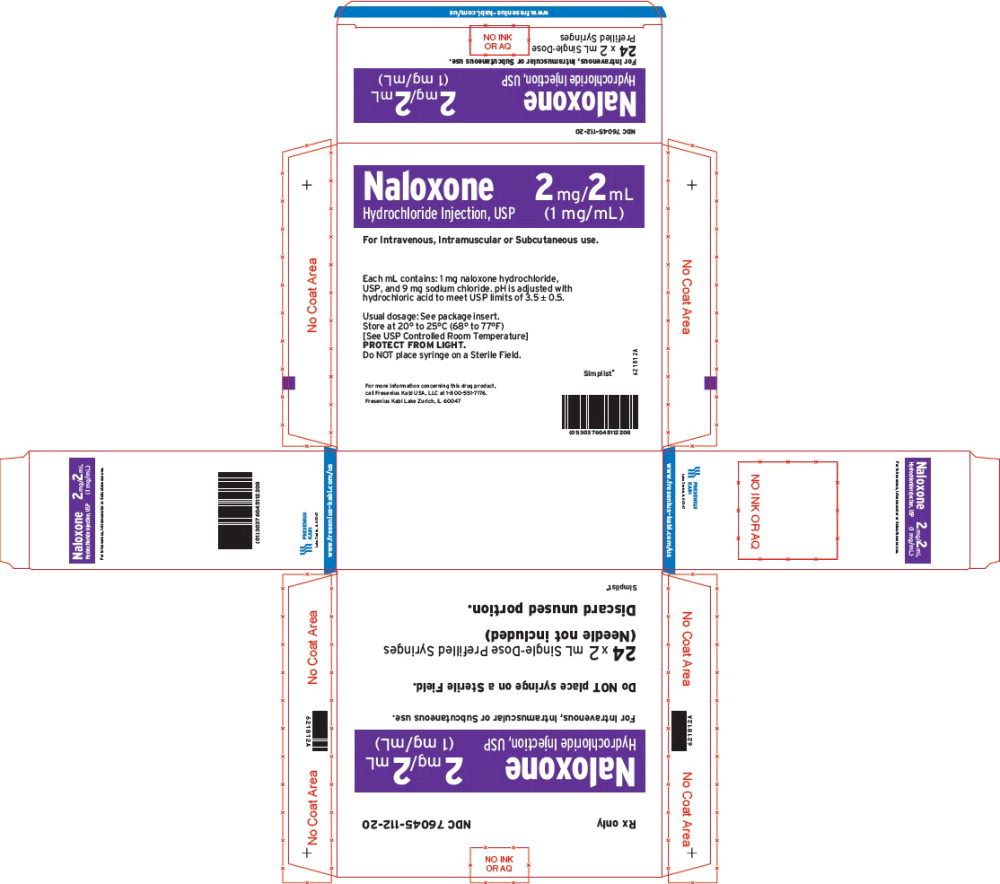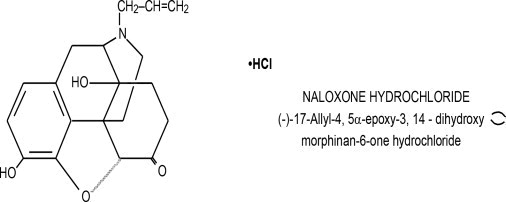 DRUG LABEL: Naloxone Hydrochloride
NDC: 76045-114 | Form: INJECTION, SOLUTION
Manufacturer: Fresenius Kabi USA, LLC
Category: prescription | Type: HUMAN PRESCRIPTION DRUG LABEL
Date: 20250731

ACTIVE INGREDIENTS: NALOXONE HYDROCHLORIDE 0.4 mg/1 mL
INACTIVE INGREDIENTS: SODIUM CHLORIDE 9 mg/1 mL; HYDROCHLORIC ACID

Naloxone Hydrochloride Injection, USP

Opioid Antagonist

Rx only

DESCRIPTION

Naloxone Hydrochloride Injection, USP, an opioid antagonist, is a synthetic congener of oxymorphone. In structure it differs from oxymorphone in that the methyl group on the nitrogen atom is replaced by an allyl group.

Naloxone hydrochloride occurs as a white to slightly off-white powder, and is soluble in water, in dilute acids, and in strong alkali; slightly soluble in alcohol; practically insoluble in ether and in chloroform.

Naloxone Hydrochloride Injection is available as a sterile solution for intravenous, intramuscular and subcutaneous administration in two concentrations: 0.4 mg and 1 mg of naloxone hydrochloride per mL.

pH is adjusted to 3.5 ± 0.5 with hydrochloric acid.

The 0.4 mg/mL prefilled syringe is available in an unpreserved, paraben-free formulation containing 9 mg/mL of sodium chloride.

The 1 mg/mL prefilled syringe is available in an unpreserved, paraben-free formulation containing 9 mg/mL of sodium chloride.

CLINICAL PHARMACOLOGY

Complete or Partial Reversal of Opioid Depression

Naloxone prevents or reverses the effects of opioids including respiratory depression, sedation and hypotension. Also, Naloxone can reverse the psychotomimetic and dysphoric effects of agonist-antagonists such as pentazocine.

Naloxone is an essentially pure opioid antagonist, i.e., it does not possess the “agonistic” or morphine-like properties characteristic of other opioid antagonists. When administered in usual doses and in the absence of opioids or agonistic effects of other opioid antagonists, it exhibits essentially no pharmacologic activity.

Naloxone has not been shown to produce tolerance or cause physical or psychological dependence. In the presence of physical dependence on opioids, Naloxone will produce withdrawal symptoms. However, in the presence of opioid dependence, opiate withdrawal symptoms may appear within minutes of Naloxone administration and subside in about 2 hours. The severity and duration of the withdrawal syndrome are related to the dose of Naloxone and to the degree and type of opioid dependence.

While the mechanism of action of Naloxone is not fully understood, in vitro evidence suggests that Naloxone antagonizes opioid effects by competing for the μ, κ and σ opiate receptor sites in the CNS, with the greatest affinity for the μ receptor.

When Naloxone is administered intravenously (I.V.), the onset of action is generally apparent within two minutes. The onset of action is slightly less rapid when it is administered subcutaneously (S.C.) or intramuscularly (I.M.). The duration of action is dependent upon the dose and route of administration of Naloxone. Intramuscular administration produces a more prolonged effect than intravenous administration. Since the duration of action of Naloxone may be shorter than that of some opiates, the effects of the opiate may return as the effects of Naloxone dissipates. The requirement for repeat doses of Naloxone will also be dependent upon the amount, type and route of administration of the opioid being antagonized.

Adjunctive Use in Septic Shock

Naloxone has been shown in some cases of septic shock to produce a rise in blood pressure that may last up to several hours; however, this pressor response has not been demonstrated to improve patient survival. In some studies, treatment with Naloxone in the setting of septic shock has been associated with adverse effects, including agitation, nausea and vomiting, pulmonary edema, hypotension, cardiac arrhythmias, and seizures. The decision to use Naloxone in septic shock should be exercised with caution, particularly in patients who may have underlying pain or have previously received opioid therapy and may have developed opioid tolerance.

Because of the limited number of patients who have been treated, optimal dosage and treatment regimens have not been established.

PHARMACOKINETICS

Distribution

Following parenteral administration, Naloxone is rapidly distributed in the body and readily crosses the placenta. Plasma protein binding occurs but is relatively weak.

Plasma albumin is the major binding constituent but significant binding of naloxone also occurs to plasma constituents other than albumin. It is not known whether naloxone is excreted into human milk.

Metabolism and Elimination

Naloxone is metabolized in the liver, primarily by glucuronide conjugation with naloxone-3-glucoronide as the major metabolite. In one study the serum half-life in adults ranged from 30 to 81 minutes (mean 64 ± 12 minutes). In a neonatal study the mean plasma half-life was observed to be 3.1 ± 0.5 hours. After an oral or intravenous dose, about 25-40% of the drug is excreted as metabolites in urine within 6 hours, about 50% in 24 hours, and 60-70% in 72 hours.

INDICATIONS AND USAGE

Naloxone is indicated for the complete or partial reversal of opioid depression, including respiratory depression, induced by natural and synthetic opioids, including propoxyphene, methadone and certain mixed agonist-antagonist analgesics: nalbuphine, pentazocine, butorphanol, and cyclazocine. Naloxone is also indicated for diagnosis of suspected or known acute opioid overdosage.

Naloxone may be useful as an adjunctive agent to increase blood pressure in the management of septic shock (see CLINICAL PHARMACOLOGY; Adjunctive Use in Septic Shock).

CONTRAINDICATIONS

Naloxone is contraindicated in patients known to be hypersensitive to naloxone hydrochloride or to any of the other ingredients in Naloxone.

WARNINGS

Drug Dependence

Naloxone should be administered cautiously to persons including newborns of mothers who are known or suspected to be physically dependent on opioids. In such cases an abrupt and complete reversal of opioid effects may precipitate an acute withdrawal syndrome.

The signs and symptoms of opioid withdrawal in a patient physically dependent on opioids may include, but are not limited to, the following: body aches, diarrhea, tachycardia, fever, runny nose, sneezing, piloerection, sweating, yawning, nausea or vomiting, nervousness, restlessness or irritability, shivering or trembling, abdominal cramps, weakness, and increased blood pressure. In the neonate, opioid withdrawal may also include: convulsions, excessive crying, and hyperactive reflexes.

Repeat Administration

The patient who has satisfactorily responded to Naloxone should be kept under continued surveillance and repeated doses of Naloxone should be administered, as necessary, since the duration of action of some opioids may exceed that of Naloxone.

Respiratory Depression due to Other Drugs

Naloxone is not effective against respiratory depression due to non-opioid drugs and in the management of acute toxicity caused by levopropoxyphene. Reversal of respiratory depression by partial agonists or mixed agonist/antagonists, such as buprenorphine and pentazocine, may be incomplete or require higher doses of naloxone. If an incomplete response occurs, respirations should be mechanically assisted as clinically indicated.

PRECAUTIONS

General

In addition to Naloxone, other resuscitative measures such as maintenance of a free airway, artificial ventilation, cardiac massage, and vasopressor agents should be available and employed when necessary to counteract acute opioid poisoning.

Abrupt postoperative reversal of opioid depression may result in nausea, vomiting, sweating, tremulousness, tachycardia, increased blood pressure, seizures, ventricular tachycardia and fibrillation, pulmonary edema, and cardiac arrest which may result in death. Excessive doses of Naloxone in postoperative patients may result in significant reversal of analgesia and may cause agitation (see PRECAUTIONS and DOSAGE AND ADMINISTRATION; Usage in Adults-Postoperative Opioid Depression).

Several instances of hypotension, hypertension, ventricular tachycardia and fibrillation, pulmonary edema, and cardiac arrest have been reported in postoperative patients.

Death, coma, and encephalopathy have been reported as sequelae of these events. These have occurred in patients most of whom had pre-existing cardiovascular disorders or received other drugs which may have similar adverse cardiovascular effects. Although a direct cause and effect relationship has not been established, Naloxone should be used with caution in patients with pre-existing cardiac disease or patients who have received medications with potential adverse cardiovascular effects, such as hypotension, ventricular tachycardia or fibrillation, and pulmonary edema. It has been suggested that the pathogenesis of pulmonary edema associated with the use of Naloxone is similar to neurogenic pulmonary edema, i.e., a centrally mediated massive catecholamine response leading to a dramatic shift of blood volume into the pulmonary vascular bed resulting in increased hydrostatic pressures.

Drug Interactions

Large doses of Naloxone are required to antagonize buprenorphine since the latter has a long duration of action due to its slow rate of binding and subsequent slow dissociation from the opioid receptor. Buprenorphine antagonism is characterized by a gradual onset of the reversal effects and a decreased duration of action of the normally prolonged respiratory depression. The barbiturate methohexital appears to block the acute onset of withdrawal symptoms induced by naloxone in opiate addicts.

Carcinogenesis, Mutagenesis, Impairment of Fertility

Studies in animals to assess the carcinogenic potential of Naloxone have not been conducted. Naloxone was weakly positive in the Ames mutagenicity and in the in vitro human lymphocyte chromosome aberration test but was negative in the in vitro Chinese hamster V79 cell HGPRT mutagenicity assay and in the in vivo rat bone marrow chromosome aberration study. Reproduction studies conducted in mice and rats at doses 4-times and 8-times, respectively, the dose of a 50 kg human given 10 mg/day (when based on surface area or mg/m^2), demonstrated no embryotoxic or teratogenic effects due to Naloxone.

Use in Pregnancy

Teratogenic Effects:

Teratology studies conducted in mice and rats at doses 4-times and 8-times, respectively, the dose of a 50 kg human given 10 mg/day (when based on surface area or mg/m^2), demonstrated no embryotoxic or teratogenic effects due to Naloxone. There are, however, no adequate and well-controlled studies in pregnant women. Because animal reproduction studies are not always predictive of human response, Naloxone should be used during pregnancy only if clearly needed.

Non-teratogenic Effects:

Risk-benefit must be considered before Naloxone is administered to a pregnant woman who is known or suspected to be opioid-dependent since maternal dependence may often be accompanied by fetal dependence. Naloxone crosses the placenta, and may precipitate withdrawal in the fetus as well as in the mother. Patients with mild to moderate hypertension who receive naloxone during labor should be carefully monitored as severe hypertension may occur.

Use in Labor and Delivery

It is not known if Naloxone (naloxone hydrochloride injection, USP) affects the duration of labor and/or delivery. However, published reports indicated that administration of Naloxone during labor did not adversely affect maternal or neonatal status.

Nursing Mothers

It is not known whether Naloxone is excreted in human milk. Because many drugs are excreted in human milk, caution should be exercised when Naloxone is administered to a nursing woman.

Pediatric Use

Naloxone Hydrochloride Injection, USP may be administered intravenously, intramuscularly or subcutaneously in children and neonates to reverse the effects of opiates. The American Academy of Pediatrics, however, does not endorse subcutaneous or intramuscular administration in opiate intoxication since absorption may be erratic or delayed. Although the opiate-intoxicated child responds dramatically to Naloxone, he/she must be carefully monitored for at least 24 hours as a relapse may occur as Naloxone is metabolized.

When Naloxone is given to the mother shortly before delivery, the duration of its effect lasts only for the first two hours of neonatal life. It is preferable to administer Naloxone directly to the neonate if needed after delivery. Naloxone has no apparent benefit as an additional method of resuscitation in the newly born infant with intrauterine asphyxia which is not related to opioid use.

Usage in Pediatric Patients and Neonates for Septic Shock:

The safety and effectiveness of Naloxone in the treatment of hypotension in pediatric patients and neonates with septic shock have not been established. One study of two neonates in septic shock reported a positive pressor response; however, one patient subsequently died after intractable seizures.

Geriatric Use

Clinical studies of Naloxone did not include sufficient numbers of subjects aged 65 and over to determine whether they respond differently from younger subjects. Other reported clinical experience has not identified differences in responses between the elderly and younger patients. In general, dose selection for an elderly patient should be cautious, usually starting at the low end of the dosing range, reflecting the greater frequency of decreased hepatic, renal, or cardiac function, and of concomitant disease or other drug therapy.

Renal Insufficiency/Failure

The safety and effectiveness of Naloxone in patients with renal insufficiency/failure have not been established in well-controlled clinical trials. Caution should be exercised when Naloxone is administered to this patient population.

Liver Disease

The safety and effectiveness of Naloxone in patients with liver disease have not been established in well-controlled clinical trials. Caution should be exercised when Naloxone is administered to patients with liver disease.

ADVERSE REACTIONS

Postoperative

The following adverse events have been associated with the use of Naloxone in postoperative patients: hypotension, hypertension, ventricular tachycardia and fibrillation, dyspnea, pulmonary edema, and cardiac arrest. Death, coma, and encephalopathy have been reported as sequelae of these events. Excessive doses of Naloxone in postoperative patients may result in significant reversal of analgesia and may cause agitation (see PRECAUTIONS and DOSAGE AND ADMINISTRATION; Usage in Adults-Postoperative Opioid Depression).

Opioid Depression

Abrupt reversal of opioid depression may result in nausea, vomiting, sweating, tachycardia, increased blood pressure, tremulousness, seizures, ventricular tachycardia and fibrillation, pulmonary edema, and cardiac arrest which may result in death (see PRECAUTIONS).

Opioid Dependence

Abrupt reversal of opioid effects in persons who are physically dependent on opioids may precipitate an acute withdrawal syndrome which may include, but is not limited to, the following signs and symptoms: body aches, fever, sweating, runny nose, sneezing, piloerection, yawning, weakness, shivering or trembling, nervousness, restlessness or irritability, diarrhea, nausea or vomiting, abdominal cramps, increased blood pressure, tachycardia. In the neonate, opioid withdrawal may also include: convulsions; excessive crying; hyperactive reflexes (see WARNINGS).

Adverse events associated with the postoperative use of Naloxone are listed by organ system and in decreasing order of frequency as follows:

Cardiac Disorders: pulmonary edema, cardiac arrest or failure, tachycardia, ventricular fibrillation, and ventricular tachycardia. Death, coma, and encephalopathy have been reported as sequelae of these events.

Gastrointestinal Disorders: vomiting, nausea

Nervous System Disorders: convulsions, paraesthesia, grand mal convulsion

Psychiatric Disorders: agitation, hallucination, tremulousness

Respiratory, Thoracic and Mediastinal Disorders: dyspnea, respiratory depression, hypoxia

Skin and Subcutaneous Tissue Disorders: nonspecific injection site reactions, sweating

Vascular Disorders: hypertension, hypotension, hot flushes or flushing.

See also PRECAUTIONS and DOSAGE AND ADMINISTRATION; Usage in Adults; Postoperative Opioid Depression.

DRUG ABUSE AND DEPENDENCE

Naloxone is an opioid antagonist. Physical dependence associated with the use of Naloxone has not been reported. Tolerance to the opioid antagonist effect of Naloxone is not known to occur.

OVERDOSAGE

There is limited clinical experience with Naloxone overdosage in humans.

Adult Patients

In one small study, volunteers who received 24 mg/70 kg did not demonstrate toxicity. In another study, 36 patients with acute stroke received a loading dose of 4 mg/kg (10 mg/m^2/min) of Naloxone followed immediately by 2 mg/kg/hr for 24 hours. Twenty- three patients experienced adverse events associated with Naloxone use, and Naloxone was discontinued in seven patients because of adverse effects. The most serious adverse events were: seizures (2 patients), severe hypertension (1), and hypotension and/or bradycardia (3).

At doses of 2 mg/kg in normal subjects, cognitive impairment and behavioral symptoms, including irritability, anxiety, tension, suspiciousness, sadness, difficulty concentrating, and lack of appetite have been reported. In addition, somatic symptoms, including dizziness, heaviness, sweating, nausea, and stomachaches were also reported. Although complete information is not available, behavioral symptoms were reported to often persist for 2-3 days.

Pediatric Patients

Up to 11 doses of 0.2 mg of Naloxone (2.2 mg) have been administered to children following overdose of diphenoxylate hydrochloride with atropine sulfate. Pediatric reports include a 2-1/2 year-old child who inadvertently received a dose of 20 mg of Naloxone for treatment of respiratory depression following overdose with diphenoxylate hydrochloride with atropine sulfate. The child responded well and recovered without adverse sequelae. There is also a report of a 4-1/2 year-old child who received 11 doses during a 12-hour period, with no adverse sequelae.

Patient Management

Patients who experience a Naloxone overdose should be treated symptomatically in a closely supervised environment. Physicians should contact a poison control center for the most up-to-date patient management information.

DOSAGE AND ADMINISTRATION

Naloxone may be administered intravenously, intramuscularly, or subcutaneously. The most rapid onset of action is achieved by intravenous administration, which is recommended in emergency situations.

Since the duration of action of some opioids may exceed that of Naloxone, the patient should be kept under continued surveillance. Repeated doses of Naloxone should be administered, as necessary.

Intravenous Infusion

Naloxone may be diluted for intravenous infusion in normal saline or 5% dextrose solutions. The addition of 2 mg of Naloxone in 500 mL of either solution provides a concentration of 0.004 mg/mL. Mixtures should be used within 24 hours. After 24 hours, the remaining unused mixture must be discarded. The rate of administration should be titrated in accordance with the patient's response.

Naloxone should not be mixed with preparations containing bisulfite, metabisulfite, long-chain or high molecular weight anions, or any solution having an alkaline pH. No drug or chemical agent should be added to Naloxone unless its effect on the chemical and physical stability of the solution has first been established.

General

Parenteral drug products should be inspected visually for particulate matter and discoloration prior to administration whenever solution and container permit.

Usage in Adults

Opioid Overdose–Known or Suspected:

An initial dose of 0.4 mg to 2 mg of Naloxone may be administered intravenously. If the desired degree of counteraction and improvement in respiratory functions are not obtained, it may be repeated at two- to three-minute intervals. If no response is observed after 10 mg of Naloxone have been administered, the diagnosis of opioid-induced or partial opioid-induced toxicity should be questioned. Intramuscular or subcutaneous administration may be necessary if the intravenous route is not available.

Postoperative Opioid Depression:

For the partial reversal of opioid depression following the use of opioids during surgery, smaller doses of Naloxone are usually sufficient. The dose of Naloxone should be titrated according to the patient's response. For the initial reversal of respiratory depression, Naloxone should be injected in increments of 0.1 to 0.2 mg intravenously at two- to three-minute intervals to the desired degree of reversal, i.e., adequate ventilation and alertness without significant pain or discomfort. Larger than necessary dosage of Naloxone may result in significant reversal of analgesia and increase in blood pressure. Similarly, too rapid reversal may induce nausea, vomiting, sweating or circulatory stress.

Repeat doses of Naloxone may be required within one- to two-hour intervals depending upon the amount, type (i.e., short or long acting) and time interval since last administration of an opioid. Supplemental intramuscular doses have been shown to produce a longer lasting effect.

Septic Shock:

The optimal dosage of Naloxone or duration of therapy for the treatment of hypotension in septic shock patients has not been established (see CLINICAL PHARMACOLOGY).

Usage in Children

Opioid Overdose–Known or Suspected:

The usual initial dose in children is 0.01 mg/kg body weight given I.V. If this dose does not result in the desired degree of clinical improvement, a subsequent dose of 0.1 mg/kg body weight may be administered. If an I.V. route of administration is not available, Naloxone may be administered I.M. or S.C. in divided doses. If necessary, Naloxone can be diluted with sterile water for injection.

Postoperative Opioid Depression:

Follow the recommendations and cautions under Adult Postoperative Depression. For the initial reversal of respiratory depression, Naloxone should be injected in increments of 0.005 mg to 0.01 mg intravenously at two- to three-minute intervals to the desired degree of reversal.

Usage in Neonates

Opioid-induced Depression:

The usual initial dose is 0.01 mg/kg body weight administered I.V., I.M. or S.C. This dose may be repeated in accordance with adult administration guidelines for postoperative opioid depression.

HOW SUPPLIED

Naloxone Hydrochloride Injection, USP for intravenous, intramuscular and subcutaneous administration is available as:

Product Code | Unit of Sale | Strength | Each
761120 | NDC 76045-112-20 Unit of 24 | 2 mg/2 mL (1 mg/mL) | NDC 76045-112-01 2 mL Single-Dose prefilled syringe (Needle not included)
761410 | NDC 76045-114-10 Unit of 24 | 0.4 mg/mL | NDC 76045-114-01 1 mL Single-Dose prefilled syringe (Needle not included)

Store at 20º to 25ºC (68º to 77ºF) [See USP Controlled Room Temperature]. Protect from light.

INSTRUCTIONS FOR USE

Figure 1: Outer Packaging and Prefilled Syringe

NOTES:

- Do not introduce any other fluid into the syringe at any time.
- Do not dilute for IV push.
- Do not re-sterilize the syringe.
- Do not use this product on a sterile field.
- This product is for single dose only.
1. Inspect the outer packaging (blister pack) to confirm the integrity of the packaging. Do not use if the blister pack or the prefilled syringe has been damaged.
2. Remove the syringe from the outer packaging. (See Figure 2)
Figure 2
3. Visually inspect the syringe. Parenteral drug products should be inspected visually for particulate matter and discoloration prior to administration, whenever solution and container permit.
4. Twist off the syringe tip cap. Do not remove the label around the luer lock collar. (See Figure 3)
Figure 3
5. Expel air bubble(s). Adjust the dose (if applicable).
6. Administer the dose ensuring that pressure is maintained on the plunger rod during the entire administration.
7. Discard the used syringe into an appropriate receptacle.

For more information concerning this drug, please call Fresenius Kabi USA, LLC at 1-800-551-7176.

To report SUSPECTED ADVERSE REACTIONS, contact Fresenius Kabi USA, LLC at 1-800-551-7176 or FDA at 1-800-FDA-1088 or www.fda.gov/medwatch.

The brand names mentioned in this document are the trademarks of their respective owners.

www.fresenius-kabi.com/us

451691A

Revised: 05/2023

PACKAGE LABEL

PACKAGE LABEL - PRINCIPAL DISPLAY – Naloxone 1 mL Syringe Label
1 mL Single-Dose. Rx only.
Naloxone

HCl Injection, USP

0.4 mg/mL

For IV, IM, or Subcutaneous use.

PACKAGE LABEL

PACKAGE LABEL - PRINCIPAL DISPLAY – Naloxone 1 mL Print Mat Label
Rx only NDC 76045-114-01
Naloxone

Hydrochloride Injection, USP

0.4 mg/mL

For IV, IM, or Subcutaneous use.

PACKAGE LABEL

PACKAGE LABEL - PRINCIPAL DISPLAY – Naloxone 1 mL Shelf Carton Panel
Rx only NDC 76045-114-10
Naloxone

Hydrochloride Injection, USP

0.4 mg/mL

For Intravenous, Intramuscular,

or Subcutaneous use.

Do NOT place syringe on a Sterile Field.

24 x 1 mL Single-Dose Prefilled Syringes

(Needle not included)

Discard unused portion.

PACKAGE LABEL

PACKAGE LABEL - PRINCIPAL DISPLAY – Naloxone 2 mL Syringe Label
2 mL Single-Dose. For IV, IM or Subcutaneous use.

Naloxone

HCl Injection, USP

2 mg/2 mL

(1 mg/mL)

Rx only

PACKAGE LABEL

PACKAGE LABEL - PRINCIPAL DISPLAY – Naloxone 2 mL Print Mat Label
Rx only NDC 76045-112-01
Naloxone

Hydrochloride Injection, USP

2 mg/2 mL

(1 mg/mL)

For Intravenous, Intramuscular, or Subcutaneous use.

PACKAGE LABEL

PACKAGE LABEL - PRINCIPAL DISPLAY – Naloxone 2 mL Shelf Carton Panel
Rx only NDC 76045-112-20
Naloxone

Hydrochloride Injection, USP

2 mg/2 mL

(1 mg/mL)

For Intravenous, Intramuscular, or Subcutaneous use.

Do NOT place syringe on a Sterile Field.

24 x 2 mL Single-Dose Prefilled Syringes

(Needle not included)

Discard unused portion.